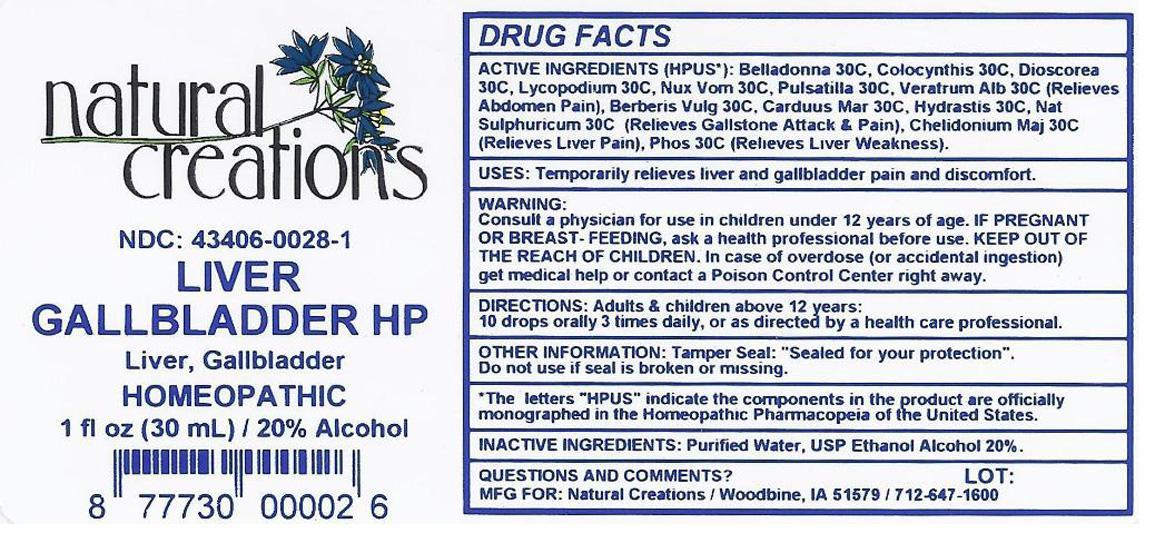 DRUG LABEL: LIVER GALLBLADDER HP
NDC: 43406-0028 | Form: LIQUID
Manufacturer: Natural Creations, Inc.
Category: homeopathic | Type: HUMAN OTC DRUG LABEL
Date: 20121105

ACTIVE INGREDIENTS: ATROPA BELLADONNA 30 [hp_X]/1 mL; CHELIDONIUM MAJUS 30 [hp_X]/1 mL; CITRULLUS COLOCYNTHIS FRUIT PULP 30 [hp_X]/1 mL; LYCOPODIUM CLAVATUM SPORE 30 [hp_X]/1 mL; SODIUM SULFATE 30 [hp_X]/1 mL; STRYCHNOS NUX-VOMICA SEED 30 [hp_X]/1 mL; PHOSPHORUS 30 [hp_X]/1 mL; PULSATILLA VULGARIS 30 [hp_X]/1 mL; VERATRUM ALBUM ROOT 30 [hp_X]/1 mL
INACTIVE INGREDIENTS: WATER; ALCOHOL

LIVER GALLBLADDER HP

ACTIVE INGREDIENT

ACTIVE INGREDIENTS (HPUS*): Belladonna 30X, Chelidonium Majus 30X, Colocynthis 30X, Lycopodium Clavatum 30X, Natrum Sulphuricum 30X, Nux Vomica 30X, Phosphorus 30X, Pulsatilla 30X, Veratrum Album 30X

INDICATIONS AND USAGE

USES: Temporarily relieves twitching, itching, pain, & tingling sensations.

WARNING:

Consult a physician for use in children under 12 years of age. IF PREGNANT OR BREAST-FEEDING, ask a health care professional before use. KEEP OUT OF THE REACH OF CHILDREN. In case of overdose (or accidental ingestion) get medical help or contact a Poison Control Center right away.

DOSAGE AND ADMINISTRATION

DIRECTIONS: Adults and children above 12 years: 10 drops orally 3 times daily, or as directed by a health care professional.

OTHER INFORMATION: Tamper Seal: "Sealed for your protection."

Do not use if seal is broken or missing.

REFERENCES

*The letters "HPUS" indicate the components in the product are officially monographed in the Homeopathic Pharmacopeia of the United States.

INACTIVE INGREDIENTS: Purified Water, USP Ethanol Alcohol 20%

QUESTIONS AND COMMENTS?

MFG FOR: Natural Creations / Woodbine, IA / 51579 712.647.1600

LOT:

PURPOSE

USES: Temporarily relieves twitching, itching, pain, & tingling sensations.

KEEP OUT OF REACH OF CHILDREN

KEEP OUT OF THE REACH OF CHILDREN. In case of overdose (or accidental ingestion) get medical help or contact a Poison Control Center.

PACKAGE LABEL

NDC: 43406-0028-1

LIVER GALLBLADDER HP

Liver * Gallbladder

HOMEOPATHIC

UPC: 877730000026